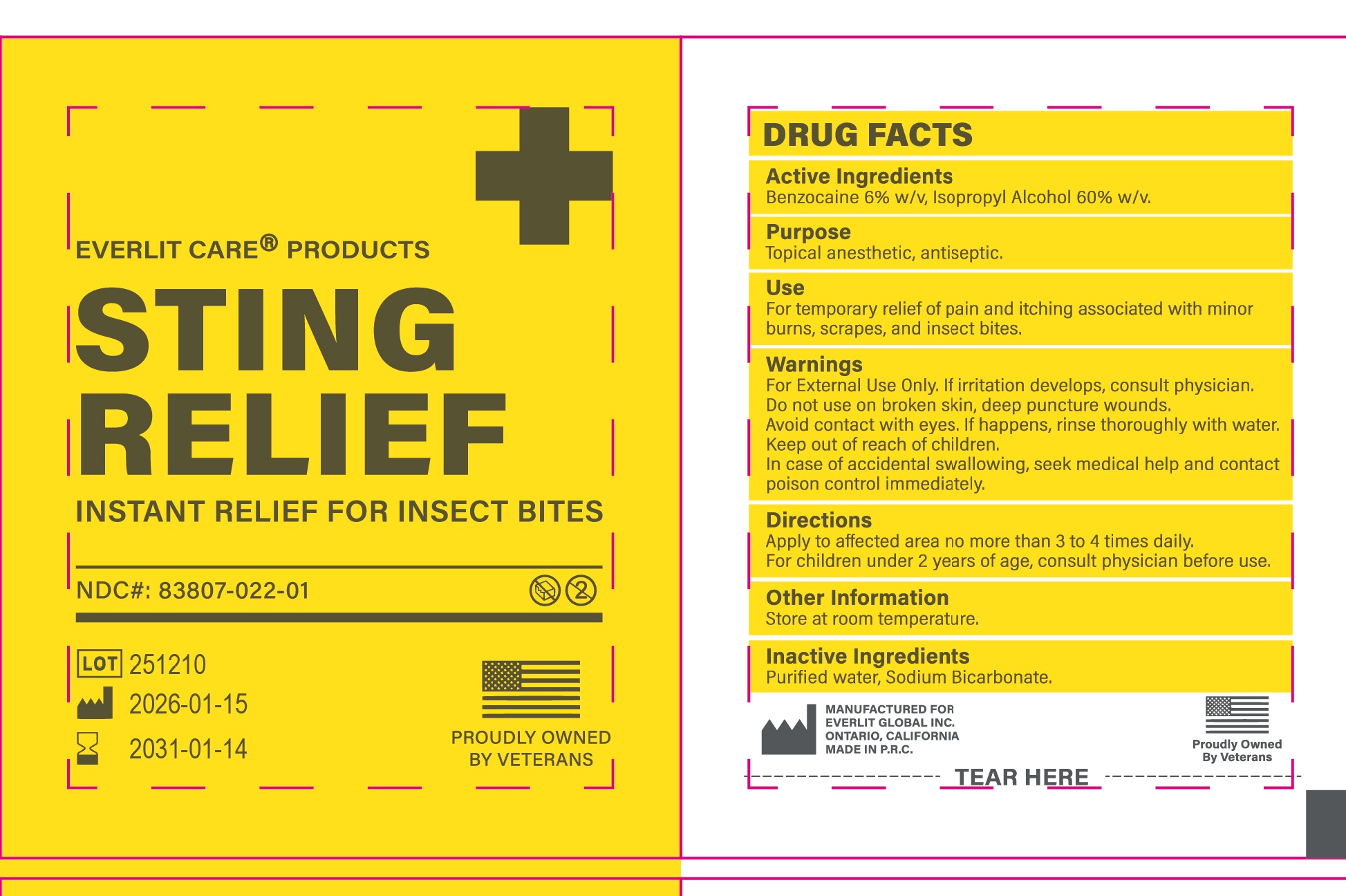 DRUG LABEL: Everlit Survival Sting Relief Pad
NDC: 83807-022 | Form: CLOTH
Manufacturer: EVERLIT GLOBAL INC.
Category: otc | Type: HUMAN OTC DRUG LABEL
Date: 20260123

ACTIVE INGREDIENTS: BENZOCAINE 0.34 g/1 1; ISOPROPYL ALCOHOL 8 g/1 1
INACTIVE INGREDIENTS: WATER; SODIUM BICARBONATE

83807-022, Everlit Survival Sting Relief Pad

ACTIVE INGREDIENT

Benocaine 6% lsopropyl Alcohol 60%

PURPOSE

Topical anesthetic, antiseptic

USES

For temporary relief of pain and itching associated with minor burns, scrapes, and insect bites

WARNINGS

For external use only. If irritation develops, consult a physician

Avoid contact with eyes. If happens, rinse thoroughly with water

Do not use on broken skin, deep puncture wounds

Keep out of reach of children. In case of accidental swallowing, seek medical help or contacta Poison Control Center immediately

Directions

Apply to affected area 3 or 4 times daily.

Children under 2 yearsof age, consult physician before use.

other Information

store at room temperature 15° - 30° C (59° - 86° F)

INACTIVE INGREDIENT

Water, Sodicum bicarbonate

Uses

For temporary relief of pain and itching associated with minor burns, scrapes, and insect bites